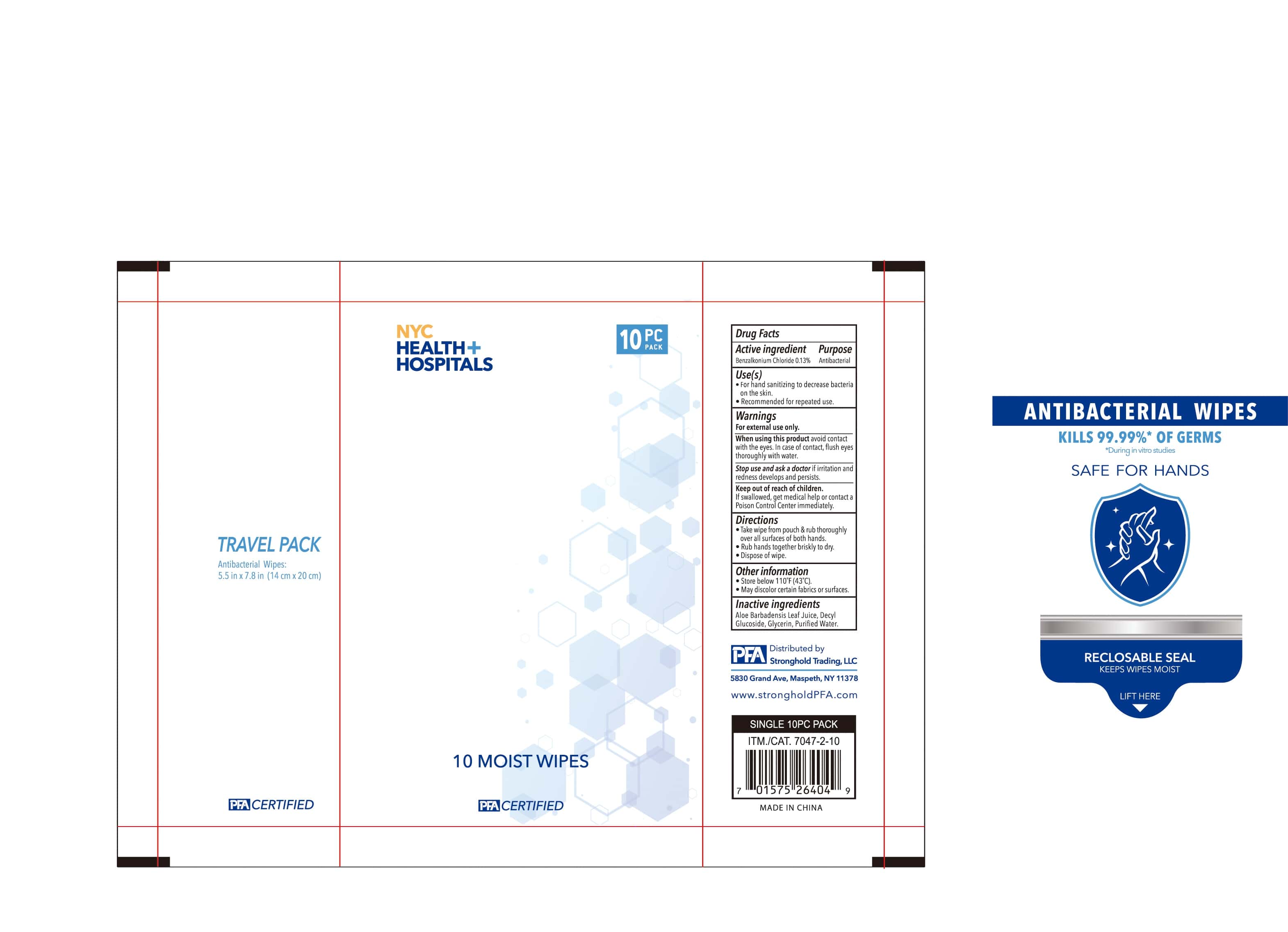 DRUG LABEL: PFA Antibacterial Wipes
NDC: 79293-003 | Form: CLOTH
Manufacturer: Hangzhou Fangyuan Textile Co., Ltd.
Category: otc | Type: HUMAN OTC DRUG LABEL
Date: 20210302

ACTIVE INGREDIENTS: BENZALKONIUM CHLORIDE 0.13 mg/1 mg
INACTIVE INGREDIENTS: DECYL GLUCOSIDE; GLYCERIN; ALOE VERA LEAF; WATER

NYC Health Hospitals Moist Wipes

Active ingredient

Benzalkonium Chloride 0.13%

Purpose

Antibacterial

Use(s)

- For hand sanitizing to decrease bacteria on the skin.
- Recommended for repeated use.

Warnings

For external use only.

When using this product avoid contact with the eyes. In case of contact, flush eyes thoroughly with water.

Stop use and ask a doctor if irritation and redness develops and persists.

Keep out of reach of children.

If swallowed, get medical help or contact a Poison Control Center immediately.

Directions

- Take wipe from pouch and rub thoroughly over all surfaces of both hands.
- Rub hands together briskly to dry.
- Dispose of wipe.

Other information

- Store below 110F (43C).
- May discolor certain fabrics or surfaces.

Inactive ingredients

Aloe Barbadensis Leaf Juice, Decyl Glucoside, Glycerin, Purified Water.

PACKAGE LABEL

10 Moist Wipes